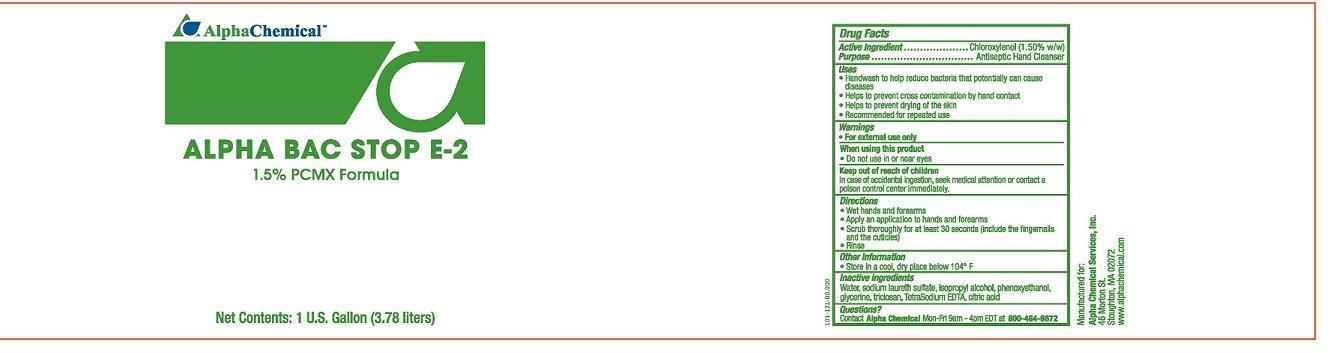 DRUG LABEL: Alpha BAC Stop E-2
NDC: 69335-001 | Form: SOLUTION
Manufacturer: Alpha Chemical Services, Inc.
Category: otc | Type: HUMAN OTC DRUG LABEL
Date: 20241216

ACTIVE INGREDIENTS: CHLOROXYLENOL 1.5 g/100 mL
INACTIVE INGREDIENTS: WATER; SODIUM LAURETH SULFATE; ISOPROPYL ALCOHOL; PHENOXYETHANOL; GLYCERIN; TRICLOSAN; EDETATE SODIUM; CITRIC ACID MONOHYDRATE

Alpha BAC STOP E-2 69335-001

Active Ingredient

Chloroxylenol (1.50% w/w)

Purpose

Antiseptic Hand Cleanser

Uses

- Handwash to help reduce bacteria that potentially can cause diseases
- Helps to prevent cross contamination by hand contact
- Helps to prevent drying of the skin
- Recommended for repated use

Warnings

- For external use only

When using this product

- Do not use in or near eyes

Keep out of reach of children

In case of accidental ingestion, seek medical attention or contact a poison control center immediately.

Directons

- Wet hands and forearms
- Apply an application to hands and forearms
- Scrub thoroughly for at least 30 seconds (include the fingernails and the cuticles)
- Rinse

Other information

- Store in a cool, dry place below 104° F

Inactive ingredients

water, sodium laureth sulfate, isopropyl alcohol, phenoxyethanol, glycerine, triclosan, TetraSodium EDTA, citric acid

Questions?

Contact Alpha Chemical Mon-Fri 9am - 4p PST at 800-464-9872

Manufactured for:

Alpha Chemical Services, Inc.

46 Morton St.

Stoughton, MA 02072

www.alphachemical.com

SDS-18-15002

Principal Display Panel

NDC: 69335-001-01

ALPHA BAC STOP E-2

1.5% PCMX FORMULA

NSF

Nonfood Compounds Program Listed (E2) Registration #